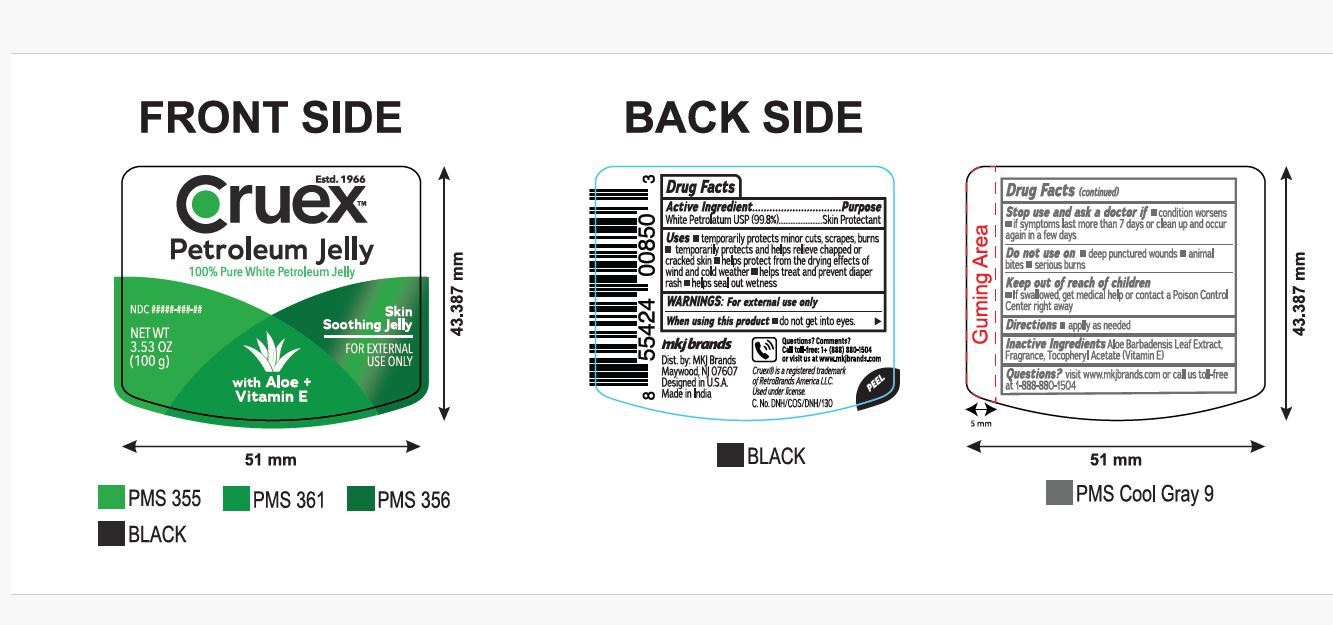 DRUG LABEL: Cruex Petroleum Jelly
NDC: 77782-003 | Form: JELLY
Manufacturer: MKJ BRANDS LLC
Category: otc | Type: HUMAN OTC DRUG LABEL
Date: 20250909

ACTIVE INGREDIENTS: PETROLATUM 99.8 g/100 g
INACTIVE INGREDIENTS: .ALPHA.-TOCOPHEROL ACETATE; ALOE BARBADENSIS LEAF

Cruex Petroleum Jelly

Drug Facts

Active Ingredient

White Petrolatum USP 99.8%

Purpose

Skin protectant

Uses

temporarily protects ■ minor cuts, scrapes,
burns ■ and help relieve chapped or cracked
skin and lips ■ from the drying effects of wind and
cold weather

-helps treat and prevent diaper rash

-helps seal out wetness

Warnings

For external use only

When using this product

do not get into eyes

Stop use and consult a doctor

if the condition lasts more than 7 days.

Do not use on

■ deep or puncture wounds
■ animal bites ■ serious burns

Keep out of reach of children

If swallowed, get medical help or contact a Poison Control Center right away. (1-800-222-1222)

Directions

apply as needed

INACTIVE INGREDIENT

Aloe barbadensis leaf extract, frafrance, tocopheryl acetate